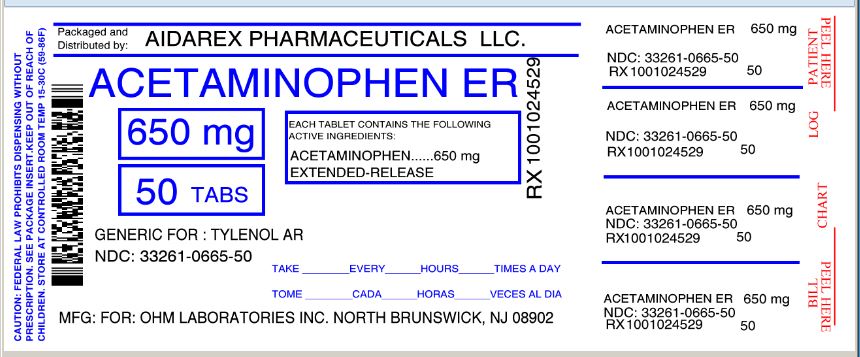 DRUG LABEL: Arthritis Pain Reliever
NDC: 33261-665 | Form: TABLET, FILM COATED, EXTENDED RELEASE
Manufacturer: Aidarex Pharmaceuticals LLC
Category: otc | Type: HUMAN OTC DRUG LABEL
Date: 20131112

ACTIVE INGREDIENTS: ACETAMINOPHEN 650 mg/1 1
INACTIVE INGREDIENTS: CROSCARMELLOSE SODIUM; HYPROMELLOSES; MAGNESIUM STEARATE; CELLULOSE, MICROCRYSTALLINE; POVIDONES; STARCH, CORN; PROPYLENE GLYCOL; SODIUM LAURYL SULFATE; STEARIC ACID; TITANIUM DIOXIDE

Drug Facts

ACTIVE INGREDIENT (IN EACH CAPLET)

Acetaminophen USP, 650 mg

PURPOSE

Pain reliever/fever reducer

USES

- temporarily relieves minor aches and pains due to:
  - minor pain of arthritis
  - muscular aches
  - backache
  - headache
  - toothache
  - the common cold
  - premenstrual and menstrual cramps

- temporarily reduces fever

WARNINGS

Liver warning: This product contains acetaminophen. Severe liver damage may occur if you take

- more than 6 caplets in 24 hours, which is the maximum daily amount
- with other drugs containing acetaminophen
- 3 or more alcoholic drinks every day while using this product

Do not use

- with any other drug containing acetaminophen (prescription or nonprescription). If you are not sure whether a drug contains acetaminophen, ask a doctor or pharmacist.
- if you are allergic to acetaminophen or any of the inactive ingredients in this product.

Ask a doctor before use if you have

liver disease.

Ask a doctor or pharmacist before use if you are

taking the blood thinning drug warfarin.

Stop use and ask a doctor if

- pain gets worse or lasts more than 10 days
- fever gets worse or lasts more than 3 days
- new symptoms occur
- redness or swelling is present

These could be signs of a serious condition.

If pregnant or breast-feeding,

ask a health professional before use.

Keep out of reach of children.

Overdose warning: In case of overdose, get medical help or contact a Poison Control Center right away (1-800-222-1222). Quick medical attention is critical for adults as well as for children even if you do not notice any signs or symptoms.

DIRECTIONS

- do not take more than directed (see overdose warning)
  adults | take 2 caplets every 8 hours with water swallow whole - do not crush, chew, split or dissolve do not take more than 6 caplets in 24 hours do not use for more than 10 days unless directed by a doctor
  under 18 years of age | ask a doctor

OTHER INFORMATION

- store at 20 - 25° C (68 - 77° F). Avoid excessive heat 40° C (104° F).
- see end panel for batch number and expiration date (Applicable only for Bottle Carton)
- TAMPER EVIDENT: DO NOT USE IF IMPRINTED SEAL IS BROKEN OR MISSING FROM BOTTLE.
- THIS PACKAGE FOR HOUSEHOLDS WITHOUT YOUNG CHILDREN. (for non CRC packages)

INACTIVE INGREDIENTS

croscarmellose sodium, hypromellose, magnesium stearate, microcrystalline cellulose, povidone, pregelatinized starch, propylene glycol, sodium lauryl sulfate, stearic acid, titanium dioxide

QUESTIONS?

call 1-800-406-7984

Contains No Aspirin

Keep the carton. It contains important information.

Distributed by:

Ohm Laboratories Inc.

1385 Livingston Avenue

North Brunswick, NJ 08902

Repackaged By :
Aidarex Pharmaceuticals LLC,
Corona, CA 92880

PRINCIPAL DISPLAY PANEL

NDC 33261-0665-50

EASY TO OPEN BOTTLE

Use only as directed.

See New Warnings Information

Lasts up to 8 hours

Arthritis Pain Relief

Acetaminophen Extended-Release Tablets, USP 650 mg

Pain Reliever/Fever Reducer

For the Temporary Relief of Minor Arthritis Pain

DO NOT USE WITH OTHER MEDICINES CONTAINING ACETAMINOPHEN

50 CAPLETS*

650 mg EACH

(* capsule-shaped tablets)

† Compare to the active ingredient of Tylenol® Arthritis Pain

† This product is not manufactured or distributed by McNeil Consumer Healthcare, Inc., The owner of the registered trademark Tylenol® is the Tylenol Company.

Repackaged By :
Aidarex Pharmaceuticals LLC,
Corona, CA 92880